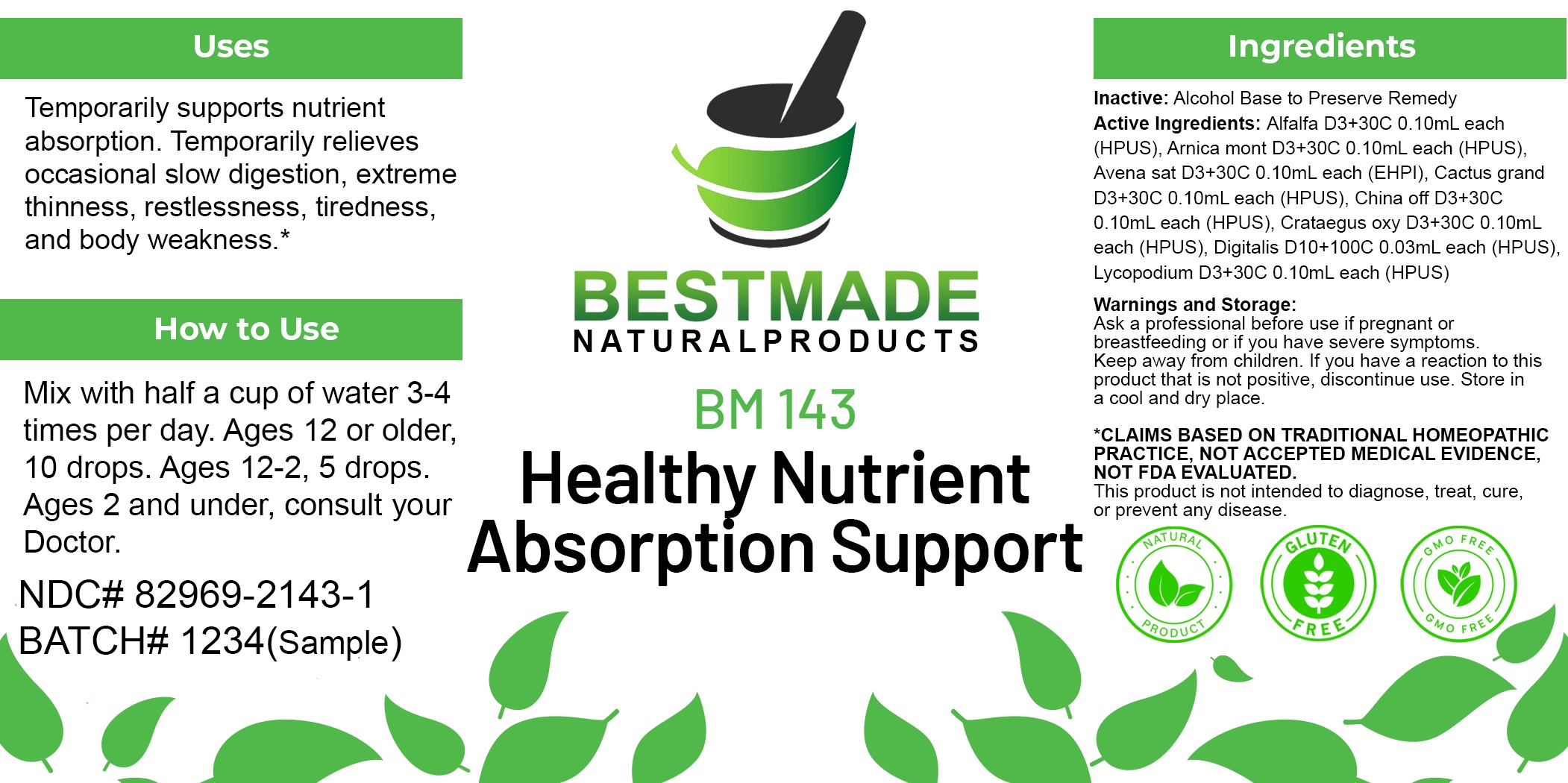 DRUG LABEL: Bestmade Natural Products BM143
NDC: 82969-2143 | Form: LIQUID
Manufacturer: Bestmade Natural Products
Category: homeopathic | Type: HUMAN OTC DRUG LABEL
Date: 20250218

ACTIVE INGREDIENTS: ARNICA MONTANA WHOLE 30 [hp_C]/30 [hp_C]; MEDICAGO SATIVA WHOLE 30 [hp_C]/30 [hp_C]; SELENICEREUS GRANDIFLORUS STEM 30 [hp_C]/30 [hp_C]; CRATAEGUS LAEVIGATA WHOLE 30 [hp_C]/30 [hp_C]; DIGITALIS 30 [hp_C]/30 [hp_C]; LYCOPODIUM CLAVATUM WHOLE 30 [hp_C]/30 [hp_C]; AVENA SATIVA FLOWERING TOP 30 [hp_C]/30 [hp_C]; CINCHONA OFFICINALIS BARK 30 [hp_C]/30 [hp_C]
INACTIVE INGREDIENTS: ALCOHOL 30 [hp_C]/30 [hp_C]

BM143

DOSAGE AND ADMINISTRATION

How to Use

Mix with half a cup of water 3-4 times per day. Ages 12 or older, 10 drops. Ages 12-2, 5 drops. Ages 2 and under, consult your Doctor.

Inactive:

Alcohol Base to Preserve Product

ACTIVE INGREDIENTS

Alfalfa D3+30C 0.10mL each (HPUS), Arnica mont D3+30C 0.10mL each (HPUS), Avena sat D3+30C 0.10mL each (EHPI), Cactus grand D3+30C 0.10mL each (HPUS), China off D3+30C 0.10mL each (HPUS), Crataegus oxy D3+30C 0.10mL each (HPUS), Digitalis D10+100C 0.03mL each (HPUS), Lycopodium D3+30C 0.10mL each (HPUS)

Uses
Temporarily supports nutrient absorption. Temporarily relieves occasional slow digestion, extreme thinness, restlessness, tiredness,
and body weakness.*

Uses
Temporarily supports nutrient absorption. Temporarily relieves occasional slow digestion, extreme thinness, restlessness, tiredness,
and body weakness.*

KEEP OUT OF REACH OF CHILDREN

Warnings and Storage:

Ask a professional before use if pregnant or breastfeeding or if you have severe symptoms.

Keep away from children. If you have a reaction to this product that is not positive, discontinue use. Store in a cool and dry place

*CLAIMS BASED ON TRADITIONAL HOMEOPATHIC PRACTICE, NOT ACCEPTED MEDICAL EVIDENCE NOT FDA EVALUATED.
This product is not intended to diagnose, treat, cure, or prevent any disease.

Warnings and Storage:

Ask a professional before use if pregnant or breastfeeding or if you have severe symptoms.

Keep away from children. If you have a reaction to this product that is not positive, discontinue use. Store in a cool and dry place

*CLAIMS BASED ON TRADITIONAL HOMEOPATHIC PRACTICE, NOT ACCEPTED MEDICAL EVIDENCE NOT FDA EVALUATED.
This product is not intended to diagnose, treat, cure, or prevent any disease.

Entire package label